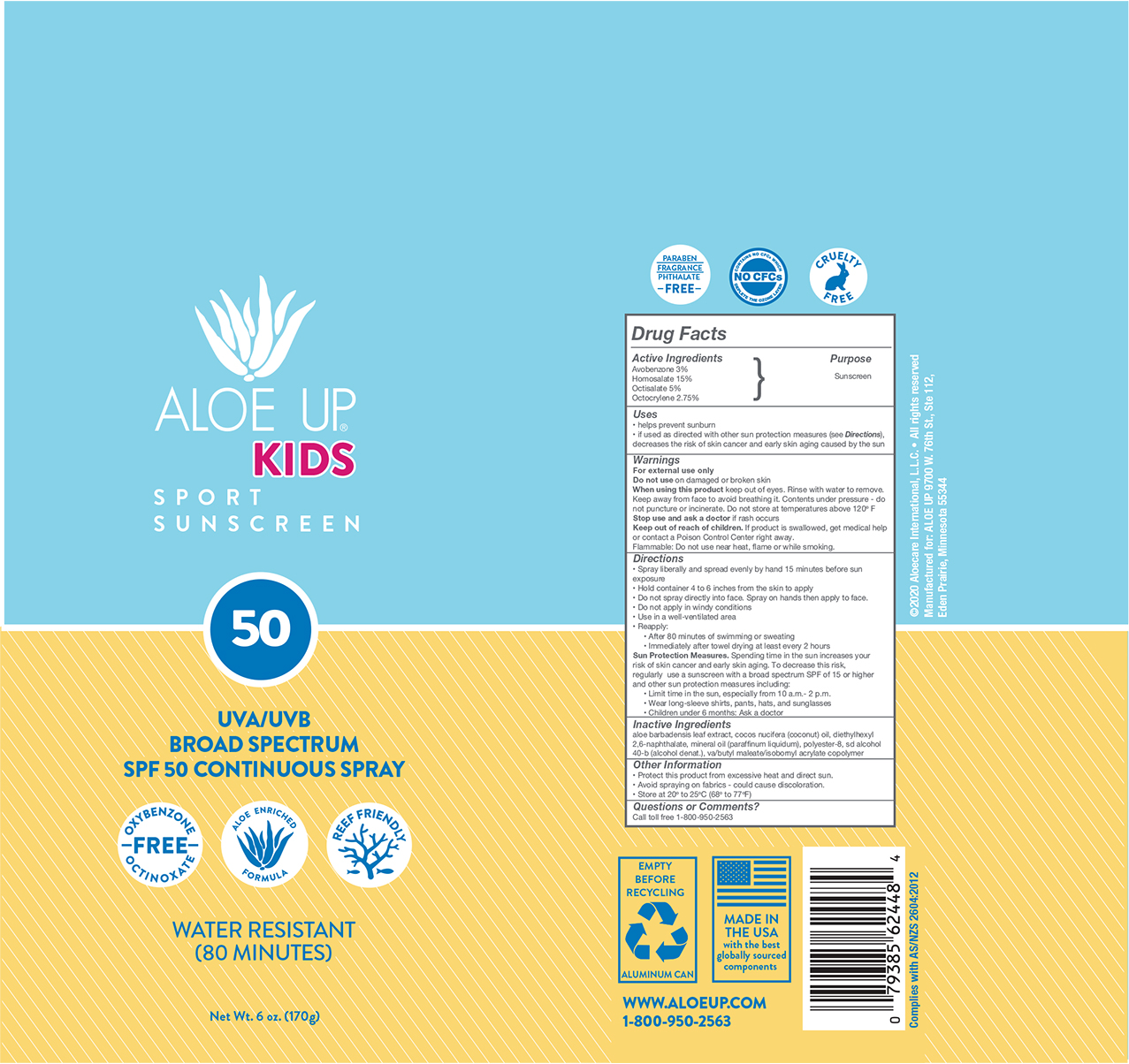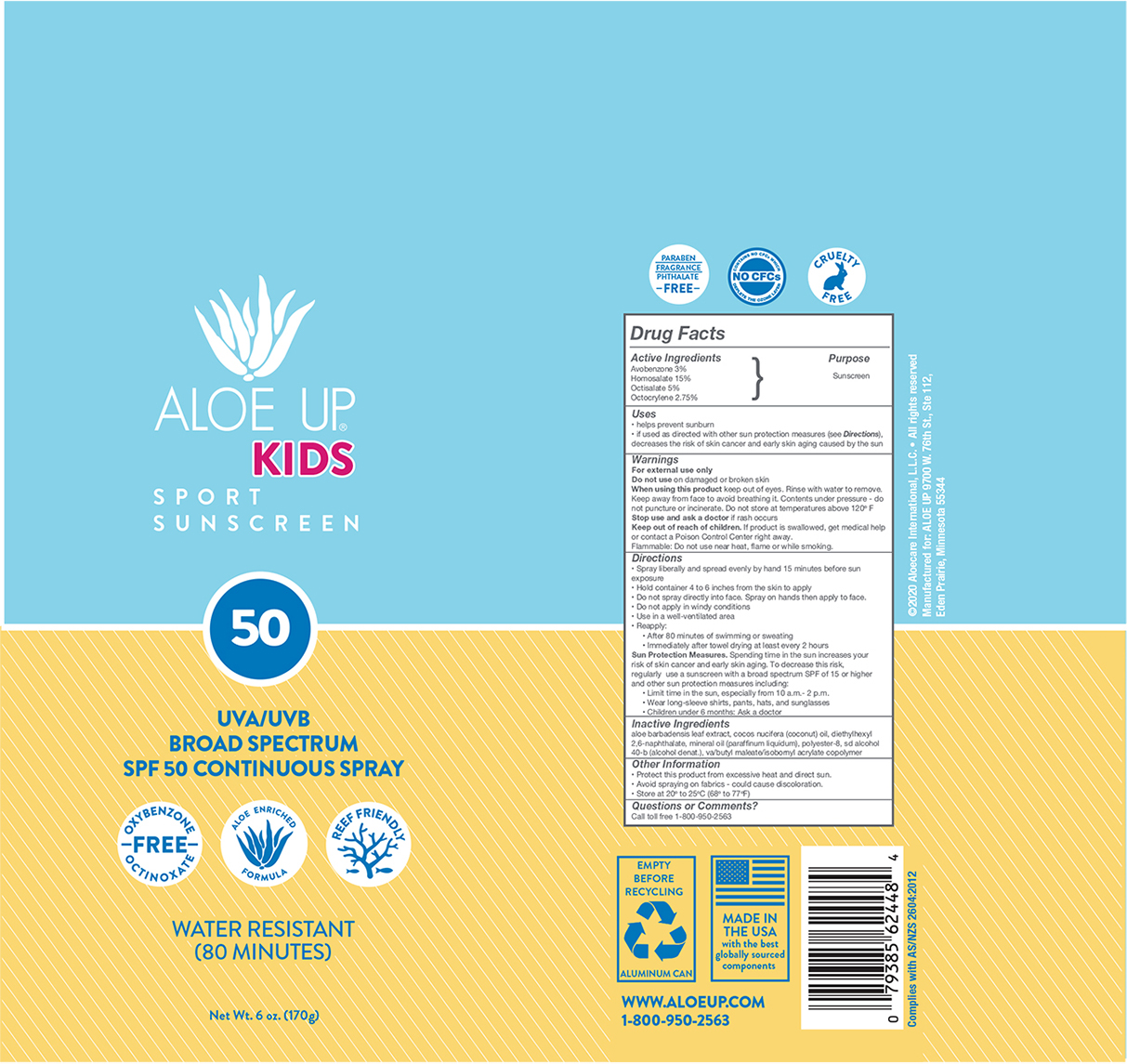 DRUG LABEL: Aloe Up Kids SPF 50
NDC: 73440-2448 | Form: AEROSOL, SPRAY
Manufacturer: Cross Brands Contract Filling
Category: otc | Type: HUMAN OTC DRUG LABEL
Date: 20210219

ACTIVE INGREDIENTS: HOMOSALATE 25.5 g/170 g; OCTOCRYLENE 4.7 g/170 g; AVOBENZONE 5.1 g/170 g; OCTISALATE 8.5 g/170 g
INACTIVE INGREDIENTS: ALCOHOL 107.5 g/170 g

Aloe Up Kids SPF 50 C-spray